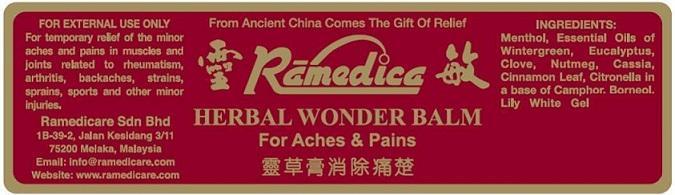 DRUG LABEL: RAMEDICA
NDC: 66059-0001 | Form: OINTMENT
Manufacturer: Ramedicare Sdn. Bhd.
Category: otc | Type: HUMAN OTC DRUG LABEL
Date: 20140220

ACTIVE INGREDIENTS: CAMPHOR (SYNTHETIC) 2.53 g/1 g; METHYL SALICYLATE 2.30 g/1 g; EUCALYPTUS OIL 2.30 g/1 g; MENTHOL 1.84 g/1 g
INACTIVE INGREDIENTS: BORNEOL 1 g/1 g; PADANG CASSIA OIL 1 g/1 g; CLOVE OIL 1 g/1 g; CINNAMON LEAF OIL 1 g/1 g; CITRONELLA OIL 1 g/1 g; NUTMEG OIL 1 g/1 g; PETROLATUM 8.03 g/1 g

Active Ingredients

Camphor

Wintergreen Oil (Methyl Salicylate)

Eucalyptus Oil

Menthol

Purpose

Topical Analgesic

Keep Out Of Reach Of Children

If swallowed, get medical help or contact a Poison Control Center immediately.

Inactive Ingredients

Borneol

Cassia Oil

Clove Oil

Cinnamon Leaf Oil

Citronella Oil

Nutmeg Oil

Petrolatum USP

Directions

For adults and children over 12, rub well on the affected area. Repeat 3 to 4 times daily

For children 12 years of age or younger, consult a doctor before use.

Warnings

For external use only. This product may cause allergic reaction in some individuals. Test on small area before use.

Uses

For temporary relief of the minor aches and pains in muscles and joints related to rheumatism, arthritis, backaches, strains, sprains, sports and other minor injuries.